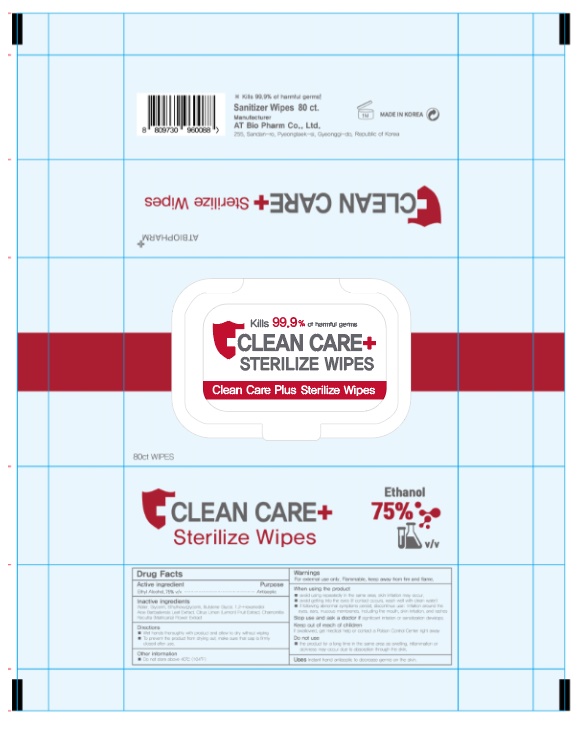 DRUG LABEL: Clean Care Plus Sterilize Wipes
NDC: 73932-0016 | Form: LIQUID
Manufacturer: AT Bio Pharm Co Ltd
Category: otc | Type: HUMAN OTC DRUG LABEL
Date: 20201103

ACTIVE INGREDIENTS: ALCOHOL 70 g/100 g
INACTIVE INGREDIENTS: LEMON OIL; ETHYLHEXYLGLYCERIN; 1,2-HEXANEDIOL; ALOE VERA LEAF; GLYCERIN; WATER; BUTYLENE GLYCOL; CHAMOMILE

Drug Facts

ACTIVE INGREDIENT

alcohol

INACTIVE INGREDIENT

Water, Glycerin, butylene glycol, ethylhexylglycerin, 1,2-hexanediol, aloe vera leaf, lemon oil, matricaria flower extract

PURPOSE

Antiseptic

instant healthcare personnel hand antiseptic to reduce bacteria that potentially can cause disease

instant hand antiseptic to decrease bacteria on the skin
recommended for repeated use

hand sanitizer to help reduce bacteria on the skin

KEEP OUT OF REACH OF THE CHILDREN

INDICATIONS AND USAGE

Apply to clean, dry hands. Apply sufficient amount to thoroughly wet all surfaces of hands and fingers. Rub onto hands until dry.

Supervise children in the use of this product.

Dispense appropriate amount on your palm and thoroughly spread on both hands and rub into the skin until dry

WARNINGS

For external use only.

Flammable, keep away from fire or flame.

When using this product keep out of eyes. If contact with eyes occurs, rinse promptly and thoroughly with water.

Stop use and ask a doctor if significant irritation or sensitization develops.

Keep out of reach of children. If swallowed, get medical help or contact a Poison Control Center right away.

DOSAGE AND ADMINISTRATION

for external use only